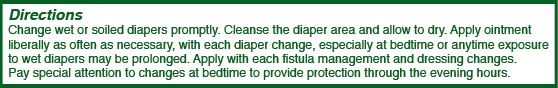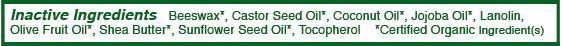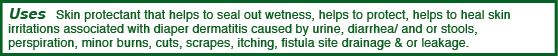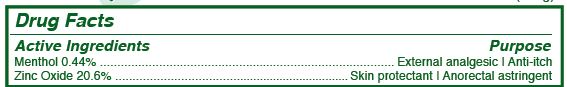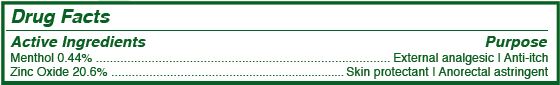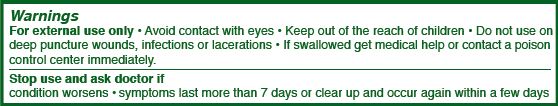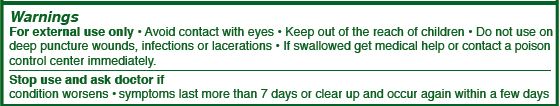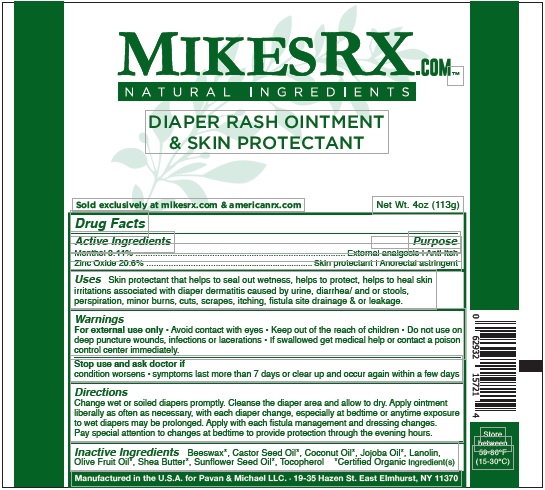 DRUG LABEL: Diaper Cream
NDC: 62932-157 | Form: OINTMENT
Manufacturer: Private Label Select Ltd CO
Category: otc | Type: HUMAN OTC DRUG LABEL
Date: 20190516

ACTIVE INGREDIENTS: MENTHOL 0.5 g/100 g; ZINC OXIDE 22 g/100 g
INACTIVE INGREDIENTS: YELLOW WAX; OLIVE OIL; JOJOBA OIL; LANOLIN; COCONUT OIL; SHEA BUTTER; CASTOR OIL; SUNFLOWER OIL; TOCOPHEROL

MikesRXment Diaper Rash Ointment